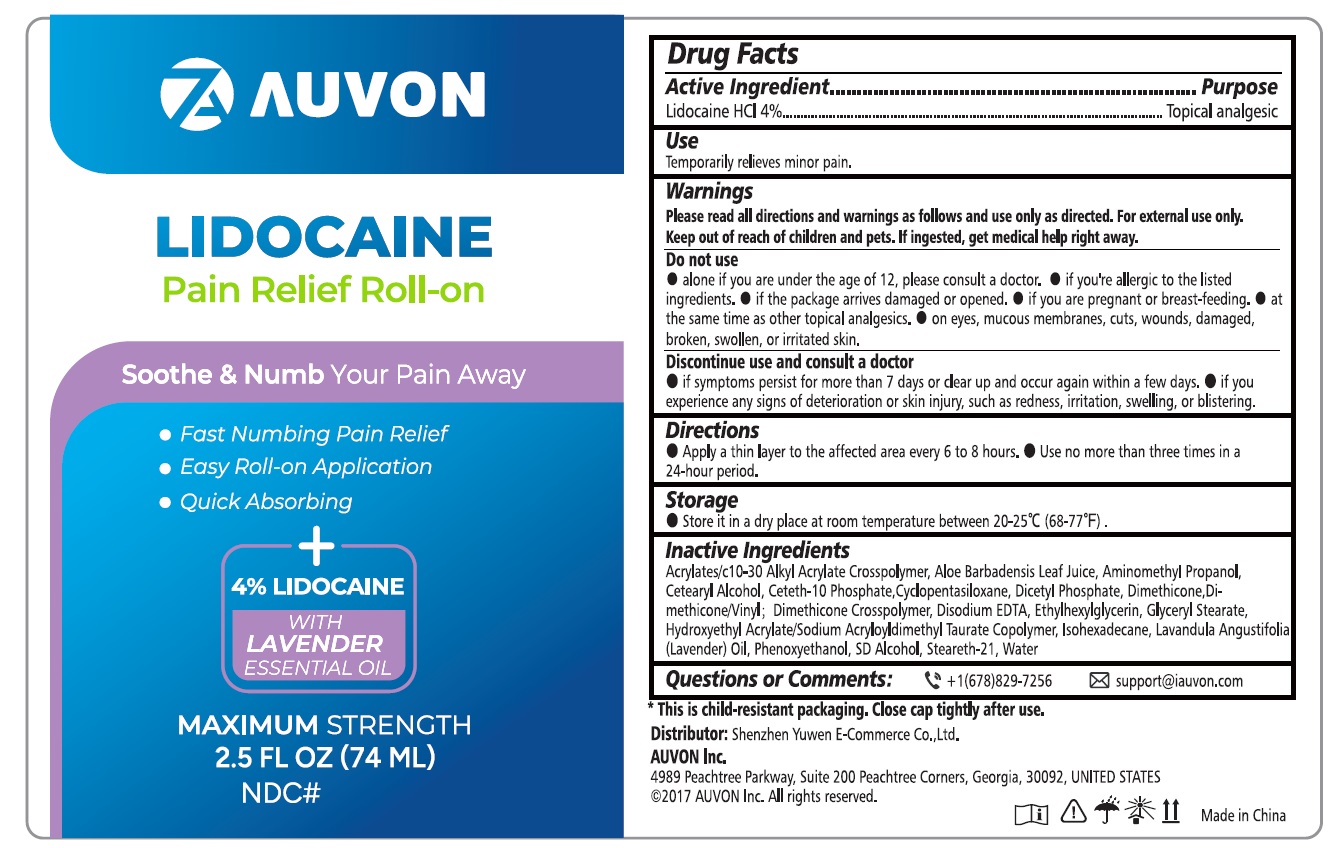 DRUG LABEL: AUVON Pain Relief Roll-on
NDC: 83391-004 | Form: SOLUTION
Manufacturer: SHENZHEN YUWEN E-COMMERCE CO., LTD.
Category: otc | Type: HUMAN OTC DRUG LABEL
Date: 20241208

ACTIVE INGREDIENTS: LIDOCAINE HYDROCHLORIDE 4 g/100 mL
INACTIVE INGREDIENTS: ACRYLATES/C10-30 ALKYL ACRYLATE CROSSPOLYMER (60000 MPA.S); WATER; ALOE VERA LEAF; CETOSTEARYL ALCOHOL; CETETH-10 PHOSPHATE; CYCLOMETHICONE 5; DIHEXADECYL PHOSPHATE; DIMETHICONE; DIMETHICONE/VINYL DIMETHICONE CROSSPOLYMER (SOFT PARTICLE); EDETATE DISODIUM ANHYDROUS; ETHYLHEXYLGLYCERIN; GLYCERYL STEARATE SE; HYDROXYETHYL ACRYLATE/SODIUM ACRYLOYLDIMETHYL TAURATE COPOLYMER (100000 MPA.S AT 1.5%); LAVENDER OIL; ISOHEXADECANE; PHENOXYETHANOL; ALCOHOL; AMINOMETHYLPROPANOL; STEARETH-21

83391-004 Lidocain Pain Relief Roll-on

AUVON Lidocaine Pain Relief Roll-on

Drug Facts

Active ingredients

Lidocaine HCl 4%

Purposes

Topical Analgestic

Use

Temporarily relieves minor pain

Warnings

Please read all directions and warnings as follows and use only as directed. For external use only

Do not use

- Alone if you are under 12 years of age, please consult a doctor
- If you are allergic to the listed ingredients
- If the package arrives damaged or opened.
- If you are pregnent or breast feeding
- At the same time as other topical analgesics
- On eyes, mucous membranes, cuts, wounds, damaged, broken, swollen, or irritated skin

Discontinue use and consult a doctor

- if symptoms persist for more than 7 days or clear up and occur again within a few days
- If you experience any signs of deterioration or skin injury, such as redness, irritation, swelling, or blistering

Keep outof reach of children and pets.

If ingested, get medical help right away.

Directions

- Apply a thin layer to the affected area every 6 to 8 hours
- Use no more than three times in a 24-hour period.

Storage

Store it in a dry place at room temperature between 20-25 C (68-77F)

Inactive ingredients

Acrylates/c10-30 Alkyl Acrylate Crosspolymer, Aloe Barbadensis Leaf Juice, AminomethyI Propanol, Cetearyl Alcohol, Ceteth-10 Phosphate,Cyclopentasiloxane, DicetyI Phosphate, Dimethicone,Dimethicone/Vinyl Dimethicone Crosspolymer, Disodium EDTA, Ethylhexylglycerin, Glyceryl Stearate, Hydroxyethyl Acrylate/Sodium Acryloyldimethyl Taurate Copolymer, Isohexadecane, Lavandula Angustifolia (Lavender) Oil, Phenoxyethanol, SD Alcohol, Steareth-21, Water